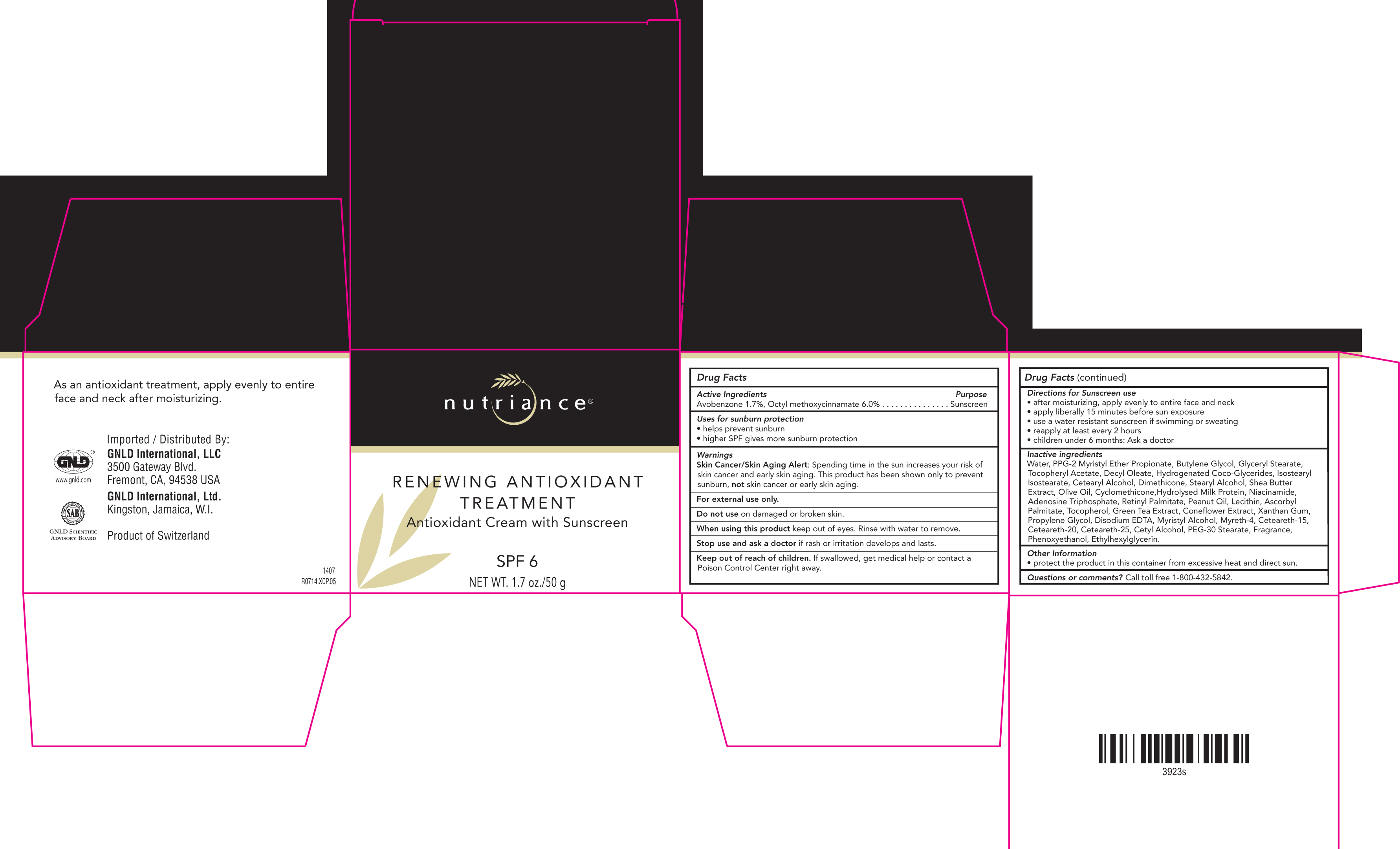 DRUG LABEL: Renewing Antioxidant  Treatment SPF 6
NDC: 76169-102 | Form: CREAM
Manufacturer: GNLD International
Category: otc | Type: HUMAN OTC DRUG LABEL
Date: 20170105

ACTIVE INGREDIENTS: OCTINOXATE 6 g/100 g; AVOBENZONE 1.7 g/100 g
INACTIVE INGREDIENTS: WATER; PPG-2 MYRISTYL ETHER PROPIONATE; BUTYLENE GLYCOL; GLYCERYL MONOSTEARATE; ALPHA-TOCOPHEROL ACETATE; DECYL OLEATE; HYDROGENATED COCO-GLYCERIDES; ISOSTEARYL ISOSTEARATE; CETOSTEARYL ALCOHOL; SHEANUT OIL; OLIVE OIL; CYCLOMETHICONE; NIACINAMIDE; ADENOSINE TRIPHOSPHATE; VITAMIN A PALMITATE; PEANUT OIL; LECITHIN, SUNFLOWER; ASCORBYL PALMITATE; TOCOPHEROL; GREEN TEA LEAF; ECHINACEA, UNSPECIFIED; XANTHAN GUM; PROPYLENE GLYCOL; EDETATE DISODIUM; MYRISTYL ALCOHOL; MYRETH-4; CETEARETH-15; CETEARETH-25; CETYL ALCOHOL; PEG-30 STEARATE; PHENOXYETHANOL; ETHYLHEXYLGLYCERIN

Nutriance Renewing Antioxidant Treatment SPF 6

Active Ingredients Purpose

Avobenzone 1.7%, Octyl methoxycinnamate 6.0% . . . . . . . . . . . . . . . Sunscreen

PURPOSE

Uses for sunburn protection

• helps prevent sunburn

• higher SPF gives more sunburn protection

Keep out of reach of children.

If swallowed, get medical help or contact a Poison Control Center right away.

Stop use and ask a doctor if rash or irritation develops and lasts

Warnings

Skin Cancer/Skin Aging Alert: Spending time in the sun increases your risk of skin cancer and early skin aging. This product has been shown to only prevent sunburn, not skin cancer or early skin aging.

For External use only

Do not use on damaged or broken skin.

When using this product, keep out of eyes. Rinse with water to remove

DOSAGE AND ADMINISTRATION

Directions for Sunscreen use

• after moisturizing, apply evenly to entire face and neck

• apply liberally 15 minutes before sun exposure

• use a water resistant sunscreen if swimming or sweating

• reapply at least every 2 hours

• children under 6 months: Ask a doctor

Inactive ingredients

Water, PPG-2 Myristyl Ether Propionate, Butylene Glycol, Glyceryl Stearate, Tocopheryl Acetate, Decyl Oleate, Hydrogenated Coco-Glycerides, Isostearyl Isostearate, Cetearyl Alcohol, Dimethicone, Stearyl Alcohol, Shea Butter Extract, Olive Oil, Cyclomethicone,Hydrolysed Milk Protein, Niacinamide, Adenosine Triphosphate, Retinyl Palmitate, Peanut Oil, Lecithin, Ascorbyl Palmitate, Tocopherol, Green Tea Extract, Coneflower Extract, Xanthan Gum, Propylene Glycol, Disodium EDTA, Myristyl Alcohol, Myreth-4, Ceteareth-15, Ceteareth-20, Ceteareth-25, Cetyl Alcohol, PEG-30 Stearate, Fragrance, Phenoxyethanol, Ethylhexylglycerin.

PACKAGE LABEL

Nutriance

Renewing Antioxidant Treatment

Antioxidant Cream with sunscreen

SPF 6

Net Wt. 1.7 oz/50g